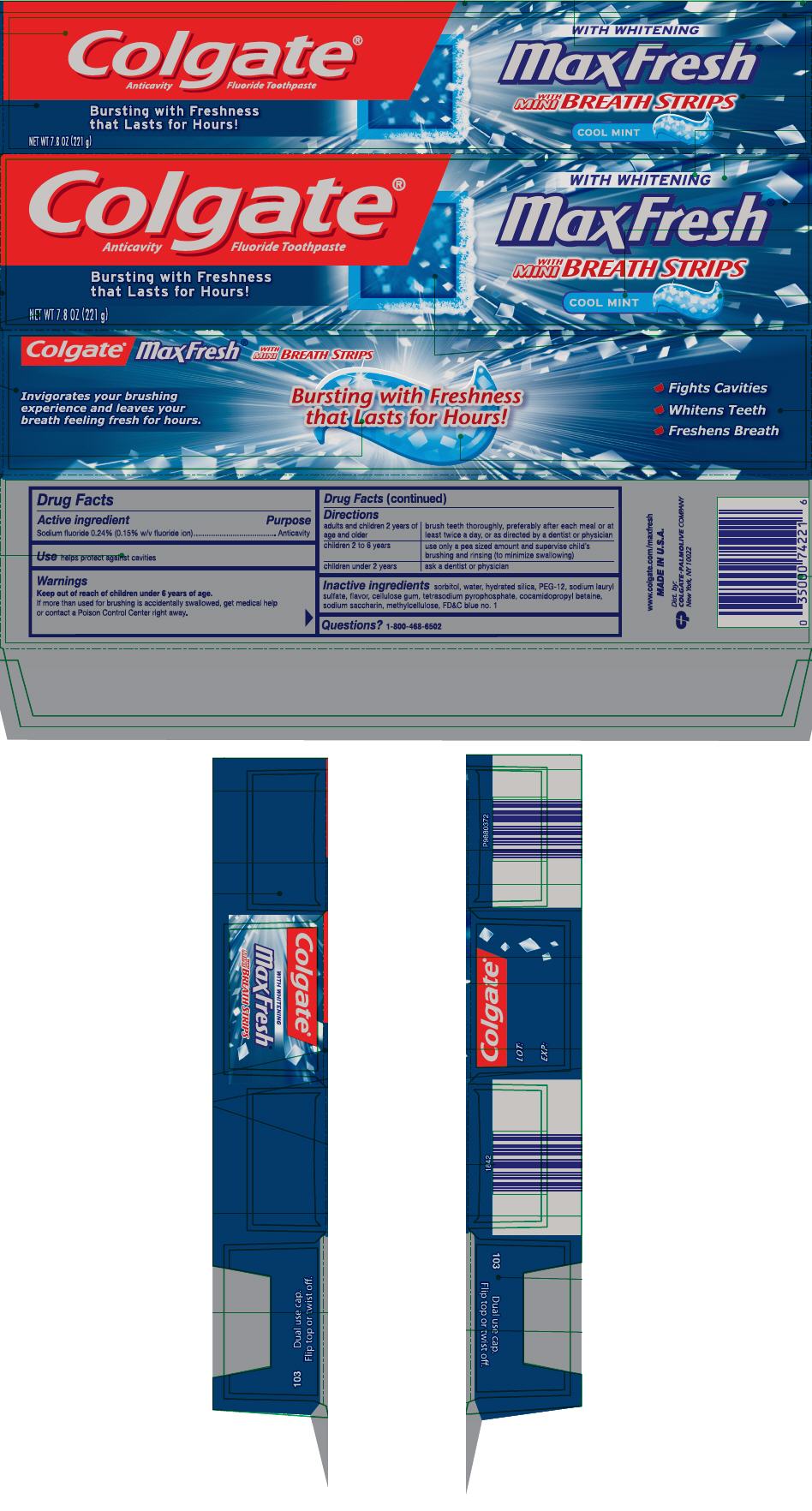 DRUG LABEL: Colgate MaxFresh with Mini Breath Cool Mint
NDC: 67659-370 | Form: PASTE, DENTIFRICE
Manufacturer: Team Technologies, Inc
Category: otc | Type: HUMAN OTC DRUG LABEL
Date: 20161206

ACTIVE INGREDIENTS: SODIUM FLUORIDE 1.4 mg/1 g
INACTIVE INGREDIENTS: SORBITOL; WATER; HYDRATED SILICA; POLYETHYLENE GLYCOL 600; SODIUM LAURYL SULFATE; CARBOXYMETHYLCELLULOSE SODIUM; SODIUM PYROPHOSPHATE; COCAMIDOPROPYL BETAINE; SACCHARIN SODIUM; METHYLCELLULOSE (100 MPA.S); FD&C BLUE NO. 1

Colgate® MaxFresh® with Mini Breath Cool Mint

Drug Facts

Active ingredient

Sodium fluoride 0.24% (0.15% w/v fluoride ion)

Purpose

Anticavity

Use

helps protect against cavities

Warnings

Keep out of reach of children under 6 years of age.

If more than used for brushing is accidentally swallowed, get medical help or contact a Poison Control Center right away.

Directions

adults and children 2 years of age and older | brush teeth thoroughly, preferably after each meal or at least twice a day, or as directed by a dentist or physician
children 2 to 6 years | use only a pea sized amount and supervise child's brushing and rinsing (to minimize swallowing)
children under 2 years | ask a dentist or physician

Inactive ingredients

sorbitol, water, hydrated silica, PEG-12, sodium lauryl sulfate, flavor, cellulose gum, tetrasodium pyrophosphate, cocamidopropyl betaine, sodium saccharin, methylcellulose, FD&C blue no. 1

Questions?

1-800-468-6502

Dist. by:
COLGATE-PALMOLIVE COMPANY
New York, NY 10022

PRINCIPAL DISPLAY PANEL - 221 g Tube Carton

Colgate®
Anticavity Fluoride Toothpaste

Bursting with Freshness
that Lasts for Hours!

NET WT 7.8 OZ (221 g)

WITH WHITENING

MaxFresh®

WITH
MINI
BREATH STRIPS

COOL MINT